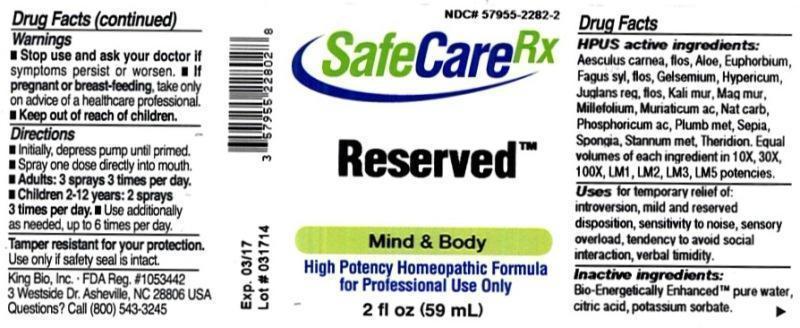 DRUG LABEL: Reserved
NDC: 57955-2282 | Form: LIQUID
Manufacturer: King Bio Inc.
Category: homeopathic | Type: HUMAN OTC DRUG LABEL
Date: 20140623

ACTIVE INGREDIENTS: AESCULUS CARNEA FLOWER 10 [hp_X]/59 mL; ALOE 10 [hp_X]/59 mL; EUPHORBIA RESINIFERA RESIN 10 [hp_X]/59 mL; FAGUS SYLVATICA FLOWERING TOP 10 [hp_X]/59 mL; GELSEMIUM SEMPERVIRENS ROOT 10 [hp_X]/59 mL; HYPERICUM PERFORATUM 10 [hp_X]/59 mL; JUGLANS REGIA FLOWERING TOP 10 [hp_X]/59 mL; POTASSIUM CHLORIDE 10 [hp_X]/59 mL; MAGNESIUM CHLORIDE 10 [hp_X]/59 mL; ACHILLEA MILLEFOLIUM 10 [hp_X]/59 mL; HYDROCHLORIC ACID 10 [hp_X]/59 mL; SODIUM CARBONATE 10 [hp_X]/59 mL; PHOSPHORIC ACID 10 [hp_X]/59 mL; LEAD 10 [hp_X]/59 mL; SEPIA OFFICINALIS JUICE 10 [hp_X]/59 mL; SPONGIA OFFICINALIS SKELETON, ROASTED 10 [hp_X]/59 mL; TIN 10 [hp_X]/59 mL; THERIDION CURASSAVICUM 10 [hp_X]/59 mL
INACTIVE INGREDIENTS: WATER; CITRIC ACID MONOHYDRATE; POTASSIUM SORBATE

Reserved™

Drug Facts

___________________________________________________________________________________________________________

HPUS active ingredients: Aesculus carnea, flos, Aloe socotrina, Euphorbium officinarum, Fagus sylvatica, flos, Gelsemium sempervirens, Hypericum perforatum, Juglans regia, flos, Kali muriaticum, Magnesia muriatica, Millefolium, Muriaticum acidum, Natrum carbonicum, Phosphoricum acidum, Plumbum metallicum, Sepia, Spongia tosta, Stannum metallicum, Theridion. Equal volumes of each ingredient in 10X, 30X, 100X, LM1, LM2, LM3, LM5 potencies.

INDICATIONS AND USAGE

Uses for temporary relief of: introversion, mild and reserved disposition, sensitivity to noise, sensory overload, tendency to avoid social interaction, verbal timidity.

INACTIVE INGREDIENT

Inactive ingredients: Bio-Energetically Enhanced™ pure water, citric acid, potassium sorbate.

Warnings

- Stop use and ask a doctor if symptoms persist or worsen.
- If pregnant or breast-feeding, take only on advice of a healthcare prodessional.

- Keep out of reach of children.

Directions:

- Initially, depress pump until primed.
- Spray one dose directly into mouth.
- Adults: 3 sprays 3 times per day.
- Children 2-12 years: 2 sprays 3 times per day.
- Use additionally as needed, up to 6 times per day.

OTHER SAFETY INFORMATION

Tamper resistant for your protection. Use only if safety seal is intact.

PURPOSE

Uses for temporary relief of:

- introversion
- mild and reserved disposition
- sensitivity to noise
- sensory overload
- tendency to avoid social interaction
- verbal timidity